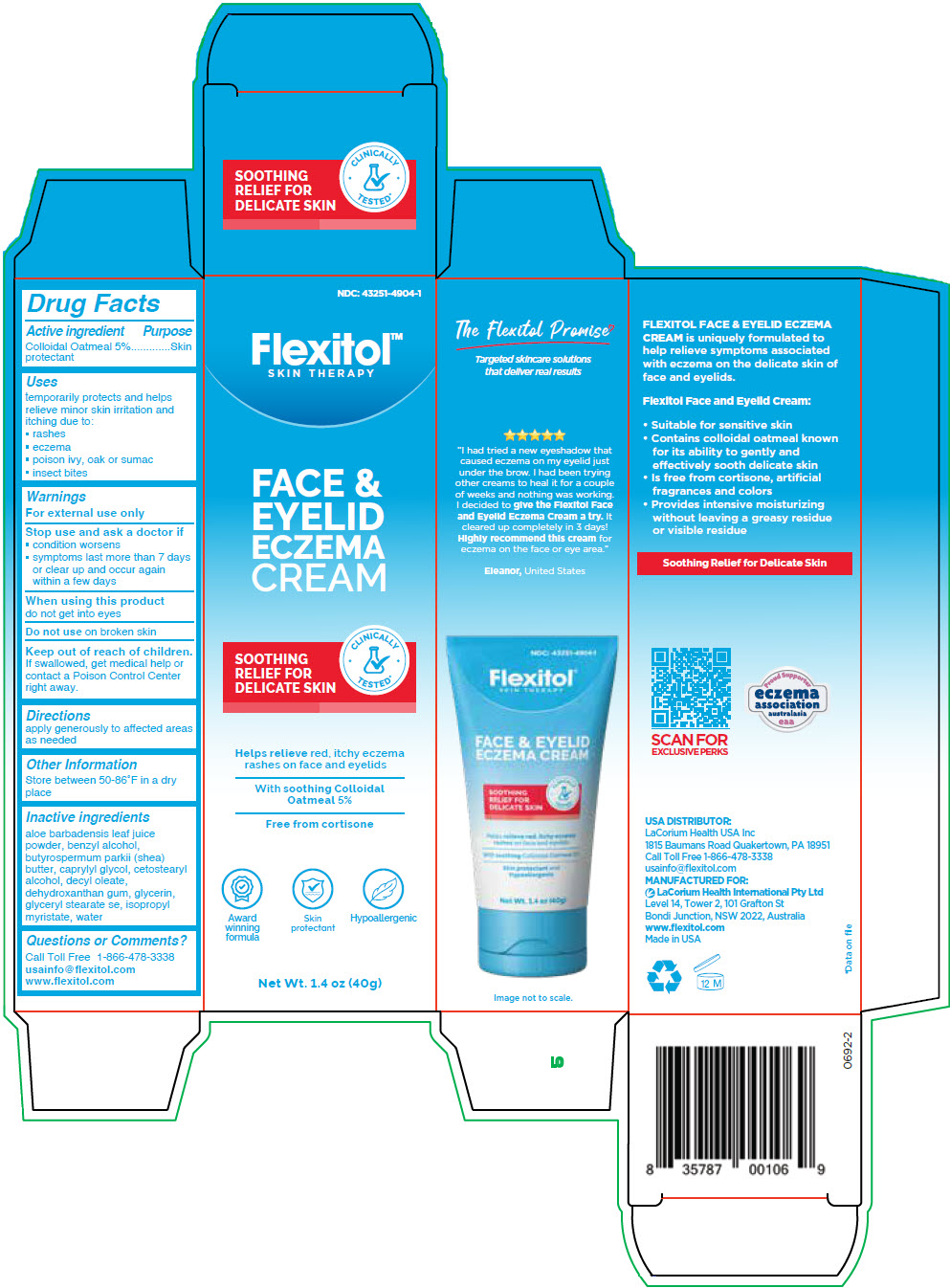 DRUG LABEL: Flexitol Face and Eyelid Eczema
NDC: 43251-4904 | Form: CREAM
Manufacturer: LaCorium Health USA Inc.
Category: otc | Type: HUMAN OTC DRUG LABEL
Date: 20251202

ACTIVE INGREDIENTS: oatmeal 50 mg/1 g
INACTIVE INGREDIENTS: Water; Cetostearyl Alcohol; GLYCERYL STEARATE SE; Isopropyl Myristate; DECYL OLEATE; Glycerin; BENZYL ALCOHOL; SHEA BUTTER; Caprylyl glycol; Dehydroxanthan gum; ALOE VERA LEAF

Flexitol® Face & Eyelid Eczema Cream

Drug Facts

Active ingredient

Colloidal Oatmeal 5%

Purpose

Skin protectant

Uses

temporarily protects and helps relieve minor skin irritation and itching due to:

- rashes
- eczema
- poison ivy, oak or sumac
- insect bites

Warnings

For external use only

Stop use and ask a doctor if

- condition worsens
- symptoms last more than 7 days or clear up and occur again within a few days

When using this product do not get into eyes

Do not use on broken skin

Keep out of reach of children.

If swallowed, get medical help or contact a Poison Control Center right away.

Directions

apply generously to affected areas as needed

Other Information

Store between 50-86°F in a dry place

Inactive ingredients

aloe barbadensis leaf juice powder, benzyl alcohol, butyrospermum parkii (shea) butter, caprylyl glycol, cetostearyl alcohol, decyl oleate, dehydroxanthan gum, glycerin, glyceryl stearate se, isopropyl myristate, water

Questions or Comments?

Call Toll Free 1-866-478-3338

usainfo@flexitol.com
www.flexitol.com

DISTRIBUTED BY:
LaCorium Health USA Inc
801 Broad St, Suite 600
Chattanooga, TN 37402

PRINCIPAL DISPLAY PANEL - 40 g Tube Carton

NDC: 43251-4904-1

Flexitol™
SKIN THERAPY

FACE &
EYELID
ECZEMA
CREAM

SOOTHING
RELIEF FOR
DELICATE SKIN

CLINICALLY
TESTED*

Helps relieve red, itchy eczema
rashes on face and eyelids

With soothing Colloidal
Oatmeal 5%

Free from cortisone

Award
winning
formula

Skin
protectant

Hypoallergenic

Net Wt. 1.4 oz (40g)